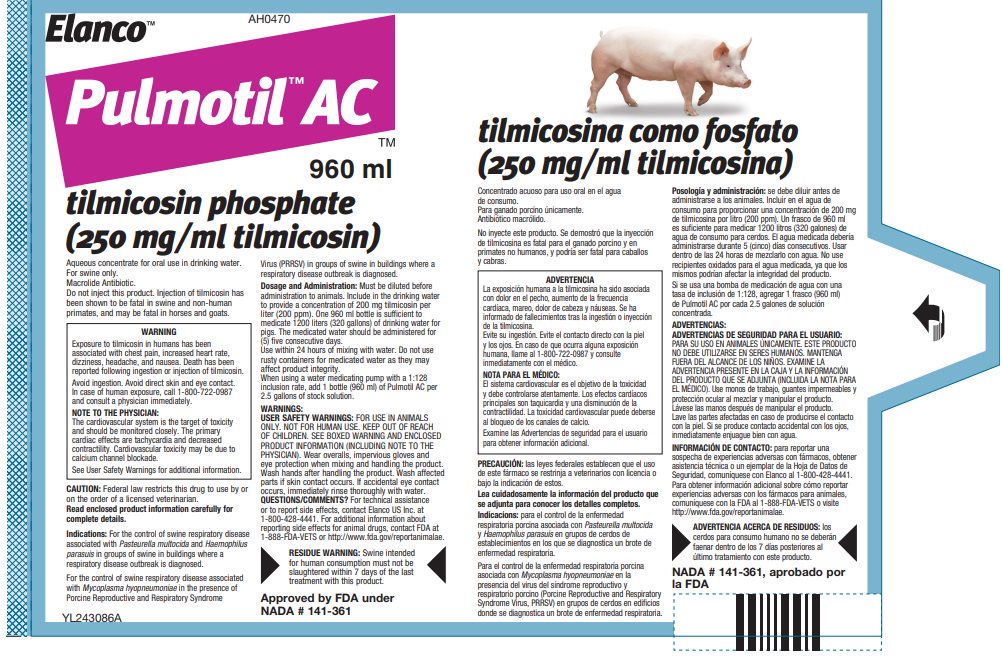 DRUG LABEL: Pulmotil AC
NDC: 58198-0470 | Form: CONCENTRATE
Manufacturer: Elanco US Inc.
Category: animal | Type: PRESCRIPTION ANIMAL DRUG LABEL
Date: 20251121

ACTIVE INGREDIENTS: tilmicosin phosphate 250 mg/1 mL

Elanco™

AH0470

960 ml

Pulmotil™AC

tilmicosin phosphate
(250 mg/ml tilmicosin)

Aqueous concentrate for oral use in drinking water.

For swine only.

Macrolide Antibiotic.

Do not inject this product. Injection of tilmicosin has been shown to be fatal in swine and non-human primates, and may be fatal in horses and goats.

WARNING

Exposure to tilmicosin in humans has been associated with chest pain, increased heart rate, dizziness, headache, and nausea. Death has been reported following ingestion or injection of tilmicosin.

Avoid ingestion. Avoid direct skin and eye contact. In case of human exposure, call 1-800-722-0987 and consult a physician immediately.

NOTE TO THE PHYSICIAN:

The cardiovascular system is the target of toxicity and should be monitored closely. The primary cardiac effects are tachycardia and decreased contractility. Cardiovascular toxicity may be due to calcium channel blockade.

See User Safety Warnings for additional information.

CAUTION: Federal law restricts this drug to use by or on the order of a licensed veterinarian.

Active Drug Ingredient: tilmicosin (as tilmicosin phosphate) 250 mg/ml

DESCRIPTION

Description: Pulmotil is a formulation of the antibiotic tilmicosin. Tilmicosin is produced semi-synthetically and is in the macrolide class of antibiotics. Each milliliter (mL) of Pulmotil aqueous concentrate solution contains 250 mg of tilmicosin.

INDICATIONS AND USAGE

Indications: For the control of swine respiratory disease associated with Pasteurella multocida and Haemophilus parasuis in groups of swine in buildings where a respiratory disease outbreak is diagnosed.

For the control of swine respiratory disease associated with Mycoplasma hyopneumoniae in the presence of Porcine Reproductive and Respiratory Syndrome Virus (PRRSV) in groups of swine in buildings where a respiratory disease outbreak is diagnosed.

Dosage and Administration: Must be diluted before administration to animals. Include in the drinking water to provide a concentration of 200 mg tilmicosin per liter (200 ppm). One 960 ml bottle is sufficient to medicate 1200 liters (320 gallons) of drinking water for pigs. The medicated water should be administered for (5) five consecutive days.

Use within 24 hours of mixing with water. Do not use rusty containers for medicated water as they may affect product integrity.

When using a water medicating pump with a 1:128 inclusion rate, add 1 bottle (960 ml) of Pulmotil AC per 2.5 gallons of stock solution.

WARNINGS:

USER SAFETY WARNINGS: FOR USE IN ANIMALS ONLY. NOT FOR HUMAN USE. KEEP OUT OF REACH OF CHILDREN. SEE BOXED WARNING AND NOTE TO THE PHYSICIAN FOR ADDITIONAL INFORMATION. Wear overalls, impervious gloves and eye protection when mixing and handling the product. Wash hands after handling the product. Wash affected parts if skin contact occurs. If accidental eye contact occurs, immediately rinse thoroughly with water.

QUESTIONS/COMMENTS? For technical assistance or to report side effects, contact Elanco US Inc. at 1-800-428-4441. For additional information about reporting side effects for animal drugs, contact FDA at 1-888-FDA-VETS or http://www.fda.gov/reportanimalae.

RESIDUE WARNING: Swine intended for human consumption must not be slaughtered within 7 days of the last treatment with this product.

Note to the Physician:

The cardiovascular system is the target of toxicity and should be monitored closely. Cardiovascular toxicity may be due to calcium channel blockade. In dogs, administration of intravenous calcium offset tilmicosin-induced tachycardia and negative inotropy (decreased contractility). Dobutamine partially offset the negative inotropic effects induced by tilmicosin injection in dogs. ß-adrenergic antagonists, such as propranolol, exacerbated the negative inotropy of tilmicosin injection in dogs. Epinephrine potentiated lethality of tilmicosin injection in pigs. This antibiotic persists in tissues for several days.

Precautions:

Do not allow horses or other equines access to water containing tilmicosin. The safety of tilmicosin has not been established in male swine intended for breeding purposes.

Always treat the fewest number of animals necessary to control a respiratory disease outbreak. Prescriptions shall not be refilled. Concurrent use of Pulmotil AC and another macrolide by any route is not advised. Use of another macrolide immediately following this use of Pulmotil AC is not advised.

ADVERSE REACTIONS

Adverse Reactions in Animals: Decreased water consumption was observed in healthy pigs administered tilmicosin in target animal safety studies. Ensure that pigs have continuous access to medicated water during the treatment period. Monitor pigs for signs of water refusal and dehydration while being treated. If decreased water consumption occurs, replace the medicated drinking water with fresh non-medicated water and contact your veterinarian.

CLINICAL PHARMACOLOGY

Clinical Pharmacology: Tilmicosin is a macrolide antibiotic with in vitro antibacterial activity primarily against Gram-positive bacteria, although certain Gram-negative bacteria are also susceptible. Macrolides interfere with bacterial protein synthesis by reversibly binding to the 50S subunit of the ribosome. They are typically regarded as being bacteriostatic, but at high concentrations can be bactericidal. When administered orally to pigs via the drinking water, tilmicosin is rapidly absorbed and slowly eliminated from the body. Tilmicosin distributes rapidly to the target tissues. Detectable levels are found in lung tissue as early as 6 hours and peak at about 5 days after the commencement of treatment. The relationship of serum tilmicosin concentration to lung tilmicosin concentration or the concentrations in bronchial secretion has not been determined. In addition, the extent to which total lung concentrations represent free (active) drug has not been defined. Therefore, no conclusions can be made with regard to the clinical relevance of elevated tilmicosin concentrations in the lung. Tilmicosin has been shown to concentrate within alveolar macrophages. It is also found at fairly high concentrations in liver and kidney tissue, as it is excreted both via the bile into the feces and also via the urine.

Effectiveness: The effectiveness of Pulmotil AC for the control of SRD associated with P. multocida and H. parasuis was confirmed in a natural infection field study across six U.S. sites. A total of 960 commercial-type grower pigs were enrolled and assigned to the tilmicosin-treated group (200 mg tilmicosin/L in drinking water for 5 consecutive days), or a non-medicated control group. Pigs that 1) were found dead and were diagnosed with SRD, or 2) had a depression score and a respiratory score ≥ 2 (on a scale from 0 [normal] to 3 [severe]) and a rectal temperature of ≥ 104.5 °F were considered clinically affected. At each site, treatments were initiated when at least 15% of the pigs were classified as clinically affected. After the 5-day treatment period and a 4-day post-treatment period, pigs were evaluated for treatment success (respiration and depression scores of 1 or 0 and rectal temperature < 104.5 °F), and were euthanized and evaluated for lung lesions. A significantly higher (p = 0.0118) success rate (based on back-transformed least squares means) was detected for the tilmicosin-treated group (275/473, 58.64%) compared to the control group (230/475, 47.89%).

The effectiveness of Pulmotil AC for the control of SRD associated with M. hyopneumoniae in the presence of PRRSV was confirmed in an induced infection model study. A total of 340 commercial-type pigs were enrolled and challenged with M. hyopneumoniae (single infection) or M. hyopneumoniae and PRRSV (co-infection). When necropsied sentinel pigs had at least 5% lung lesion involvement, study pigs were treated with Pulmotil AC (200 mg tilmicosin/L in drinking water) or non-medicated water for 5 consecutive days. After the 5-day treatment period and a 4 day post-treatment period, pigs were euthanized and evaluated for lung lesions.

For both the single infection and co-infection groups, the lung lesion percentage was statistically significantly different (p = 0.005 and p = 0.0004, respectively) in favor of the tilmicosin phosphate-treated group (21.01% and 31.74%, respectively) compared with the control group (28.26% and 43.04%, respectively).

ANIMAL PHARMACOLOGY AND OR TOXICOLOGY

Animal Safety: A pharmacokinetic study was conducted to evaluate Pulmotil AC concentrate solution in pigs. The results were compared to pharmacokinetic data generated with Pulmotil 90 Type A medicated article (NADA 141-064). The data demonstrates that blood and tissue levels of tilmicosin when administered to pigs at 200 mg/L (ppm) in water were consistently lower than when tilmicosin was administered to pigs at 181 g/ton (200 ppm) in feed.

A target animal safety study was conducted to evaluate the tolerance of Pulmotil AC concentrate solution in pigs when administered in drinking water. Twenty pigs were administered medicated water at 0, 200, 400, or 600 mg/L (0, IX, 2X, or 3X the labeled dose) for 5 consecutive days or 200 mg/L for 10 consecutive days. No treatment-related lesions were observed in any animals at necropsy. Water consumption was decreased in all tilmicosin-treated groups compared to the non-medicated group. One pig in the 600 mg/L group was euthanized due to decreased water consumption, neurological signs attributed to severe dehydration, and subsequent refusal to drink non-medicated water. Two pigs in the 400 mg/L group had reduced water intake and displayed mild clinical signs attributed to dehydration. One pig recovered after being offered non-medicated water. The second pig completed the treatment regimen without intervention.

Hydration and water consumption were evaluated during the control of SRD effectiveness field study. Tilmicosin was administered to study pigs in drinking water at 200 mg/l for 5 consecutive days. There was no statistically significant difference in water consumption between tilmicosin-treated pigs and pigs receiving non-medicated water. A subset of study pigs (20 tilmicosin-treated pigs and 20 non-medicated pigs) were evaluated for hydration via a physical examination and analysis of blood samples for hematocrit, total protein, creatinine, and blood urea nitrogen. There were no abnormal physical examination findings or clinically relevant differences in clinical pathology variables between tilmicosin-treated pigs and pigs receiving non-medicated water.

HOW SUPPLIED

How Supplied: Pulmotil AC is provided in a 960 ml amber-colored plastic bottle sealed with a plastic screw cap.

Storage Conditions:
Store at or below 86° F (30° C). Protect from direct sunlight.

Restricted Drug (California) - Use Only as Directed
Approved by FDA under NADA # 141-361

Manufactured For:
Elanco US Inc.
Indianapolis, IN 46221

Pulmotil, Elanco and the diagonal bar logo are trademarks of Elanco or its affiliates.

Elanco™

AH0470

960 ml

Pulmotil™AC

tilmicosina como fosfato
(250 mg/ml tilmicosina)

(Tilmicosina como fosfato de tilmicosina 250 mg/ml).

Concentrado acuoso para uso oral en el agua de consumo.

Para ganado porcino únicamente.

Antibiótico macrólido.

No inyecte este producto. Se demostró que la inyección de tilmicosina es fatal para el ganado porcino y en primates no humanos, y podría ser fatal para caballos y cabras.

ADVERTENCIA

La exposición humana a la tilmicosina ha sido asociada con dolor en el pecho, aumento de la frecuencia cardíaca, mareo, dolor de cabeza y náuseas. Se ha informado de fallecimientos tras la ingestión o inyección de la tilmicosina.

Evite su ingestión. Evite el contacto directo con la piel y los ojos. En caso de que ocurra alguna exposición humana, llame al 1-800-722-0987 y consulte inmediatamente con el médico.

NOTA PARA EL MÉDICO:

El sistema cardiovascular es el objetivo de la toxicidad y debe controlarse atentamente. Los efectos cardíacos principales son taquicardia y una disminución de la contractilidad. La toxicidad cardiovascular puede deberse al bloqueo de los canales de calcio.

Examine las Advertencias de seguridad para el usuario para obtener información adicional.

PRECAUCIÓN: las leyes federales establecen que el uso de este fármaco se restrinja a veterinarios con licencia o bajo la indicación de estos.

Ingrediente fármaco activo: tilmicosina (como fosfato de tilmicosina) 250 mg/ml

DESCRIPTION

Descripción: Pulmotil es una formulación del antibiótico tilmicosina. La tilmicosina se produce en forma semisintética y pertenece a la clase de antibióticos macrólidos. Cada mililitro (ml) de solución de concentrado acuoso Pulmotil contiene 250 mg de tilmicosina.

INDICATIONS AND USAGE

Indicacions: para el control de la enfermedad respiratoria porcina asociada con Pasteurella multocida y Haemophilus parasuis en grupos de cerdos de establecimientos en los que se diagnostica un brote de enfermedad respiratoria.

Para el control de la enfermedad respiratoria porcina asociada con Mycoplasma hyopneumoniae en la presencia del virus del síndrome reproductivo y respiratorio porcino (Porcine Reproductive and Respiratory Syndrome Virus, PRRSV) en grupos de cerdos en edificios donde se diagnostica un brote de enfermedad respiratoria.

DOSAGE AND ADMINISTRATION

Posología y administración: se debe diluir antes de administrarse a los animales. Incluir en el agua de consumo para proporcionar una concentración de 200 mg de tilmicosina por litro (200 ppm). Un frasco de 960 ml es suficiente para medicar 1200 litros (320 galones) de agua de consumo para cerdos. El agua medicada debería administrarse durante 5 (cinco) días consecutivos. Usar dentro de las 24 horas de mezclarlo con agua. No use recipientes oxidados para el agua medicada, ya que los mismos podrían afectar la integridad del producto.

Si se usa una bomba de medicación de agua con una tasa de inclusión de 1:128, agregar 1 frasco (960 ml) de Pulmotil AC por cada 2.5 galones de solución concentrada.

ADVERTENCIAS:

ADVERTENCIAS DE SEGURIDAD PARA EL USUARIO: PARA SU USO EN ANIMALES ÚNICAMENTE. ESTE PRODUCTO NO DEBE UTILIZARSE EN SERES HUMANOS. MANTENGA FUERA DEL ALCANCE DE LOS NIÑOS. EXAMINE LA ADVERTENCIA Y LA NOTA PARA EL MÉDICO PARA ADICIONAL INFORMACIÓN. Use monos de trabajo, guantes impermeables y protección ocular al mezclar y manipular el producto. Lávese las manos después de manipular el producto. Lave las partes afectadas en caso de producirse el contacto con la piel. Si se produce contacto accidental con los ojos, inmediatamente enjuague bien con agua.

Para informar de una sospecha de eventos adversos, obtener asistencia técnica o una hoja de datos de seguridad del material (Material Safety Data Sheet, MSDS), llame al 1-800-428-4441.

ADVERTENCIA ACERCA DE RESIDUOS: los cerdos para consumo humano no se deberán faenar dentro de los 7 días posteriores al último tratamiento con este producto.

Nota para el médico:

El sistema cardiovascular es el objetivo de la toxicidad y debe controlarse atentamente. La toxicidad cardiovascular puede deberse al bloqueo de los canales de calcio. En los perros, la administración de calcio por vía intravenosa contrarresta la taquicardia inducida por la tilmicosina y el inotropismo negativo (disminución de la contractilidad). La dobutamina contrarresta parcialmente los efectos inotrópicos negativos inducidos por la tilmicosina en perros. Los antagonistas ß adrenérgicos, como el propranolol, exacerbaron el inotropismo negativo de la inyección de tilmicosina en perros. La epinefrina potenció la letalidad de la inyección de tilmicosina en cerdos. Este antibiótico persiste en los tejidos durante varios días.

Precauciones:

No permita que caballos u otros equinos accedan al agua que contiene tilmicosina. No se ha establecido la seguridad de la tilmicosina en cerdos machos que se usan con fines de reproducción.

Trate siempre el menor número de animales necesario para controlar un brote de enfermedad respiratoria. Las recetas no deben renovarse.

No se recomienda el uso simultáneo de Pulmotil AC y otro macrólido por cualquier vía de administración. No se recomienda el uso de otro macrólido inmediatamente después de este uso de Pulmotil AC.

ADVERSE REACTIONS

Reacciones adversas en animales: se observó una disminución en el consumo de agua en cerdos saludables a los que se administró tilmicosina en estudios de seguridad en animales objetivo. Asegúrese de que los cerdos tengan acceso constante al agua medicada durante el período de tratamiento. Controle que los cerdos no presenten signos de rechazo al agua y deshidratación mientras se los esté tratando. Si se produce una disminución en el consumo de agua, reemplace el agua de consumo medicada por agua potable sin medicar y comuníquese con su veterinario.

HOW SUPPLIED

Presentación: Pulmotil AC se proporciona en botellas de plástico, color ámbar de 960 ml selladas con tapas plásticas con rosca.

STORAGE AND HANDLING

Condiciones de almacenamiento: Almacenar a una temperatura de 86 ºF (30 ºC) o inferior. Proteger de la luz solar directa.

Fármaco restringido (California). Usar únicamente según las indicaciones.
Aprobado por la FDA bajo NADA # 141-361

Fabricado por:
Elanco US Inc.
Indianapolis, IN 46221

Pulmotil, Elanco y el logo de la barra diagonal son marcas de Elanco o sus afiliadas.

© 2025 Elanco or its affiliates

Principal Display Panel – 960 mL Bottle Label

Elanco™ AH0470

Pulmotil™ AC™

960 ml

tilmicosin phosphate
(250 mg/ml tilmicosin)